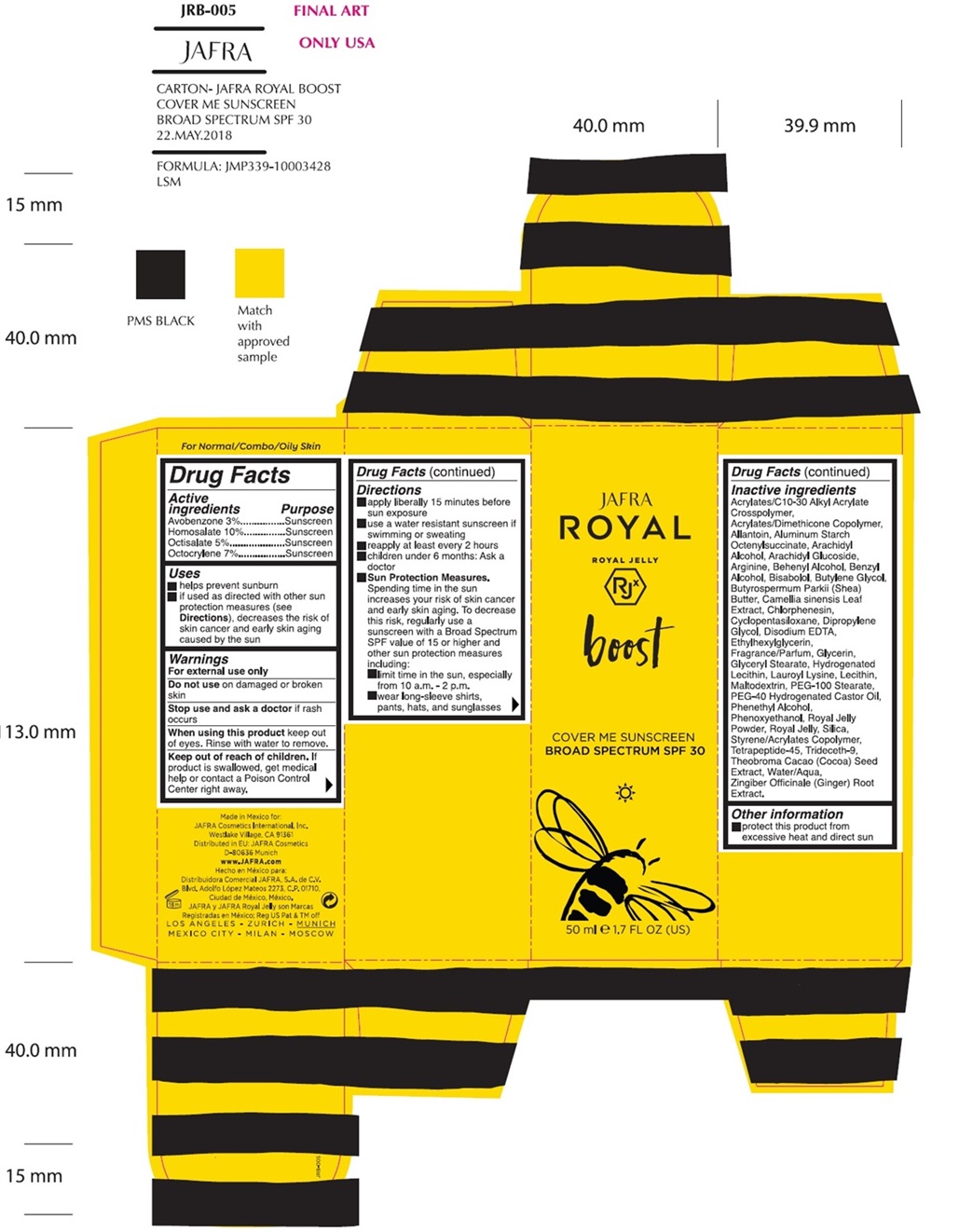 DRUG LABEL: Royal Boost Cover Me Sunscreen Broad Spectrum SPF 30
NDC: 68828-749 | Form: LOTION
Manufacturer: Distribuidora Comercial Jafra, S.A. de C.V.
Category: otc | Type: HUMAN OTC DRUG LABEL
Date: 20241219

ACTIVE INGREDIENTS: AVOBENZONE 3 g/100 mL; HOMOSALATE 10 g/100 mL; OCTISALATE 5 g/100 mL; OCTOCRYLENE 7 g/100 mL
INACTIVE INGREDIENTS: CARBOMER COPOLYMER TYPE A (ALLYL PENTAERYTHRITOL CROSSLINKED); ALLANTOIN; ALUMINUM STARCH OCTENYLSUCCINATE; ARACHIDYL ALCOHOL; ARACHIDYL GLUCOSIDE; ARGININE; DOCOSANOL; BENZYL ALCOHOL; LEVOMENOL; BUTYLENE GLYCOL; SHEA BUTTER; GREEN TEA LEAF; CHLORPHENESIN; CYCLOMETHICONE 5; DIPROPYLENE GLYCOL; EDETATE DISODIUM; ETHYLHEXYLGLYCERIN; GLYCERIN; GLYCERYL MONOSTEARATE; HYDROGENATED SOYBEAN LECITHIN; LAUROYL LYSINE; LECITHIN, SOYBEAN; MALTODEXTRIN; PEG-100 STEARATE; POLYOXYL 40 HYDROGENATED CASTOR OIL; PHENYLETHYL ALCOHOL; PHENOXYETHANOL; ROYAL JELLY; SILICON DIOXIDE; STYRENE/ACRYLAMIDE COPOLYMER (500000 MW); TRIDECETH-9; COCOA; WATER; GINGER

ROYAL BOOST COVER ME SUNSCREEN BROAD SPECTRUM SPF 30

Active ingredients Purpose
Avobenzone 3%
Homosalate 10%
Octisalate 5%
Octocrylene 7%

Purpose

Sunscreen

Uses

- Helps prevent sunburn
- If used as directed with other sun protection measures (see Directions), decreases the risk of skin cancer and early skin aging caused by the sun.

Warnings

For external use only

Do not useon damaged or broken skin

When using this productkeep out of eyes. Rinse with water to remove.

Stop use and ask a doctorif rash occurs

Keep out of reach of children.If swallowed, get medical help or contact a Poison Control Center right away.

Directions

- apply liberally 15 minutes before sun exposure
- use a water resistant sunscreen if swimming or sweating
- reapply at least every 2 hours
- children under 6 months: Ask a doctor
- Sun Protection Measures.Spending time in the sun increases your risk of skin cancer and early skin aging. To decrease this risk, regularly use a sunscreen with a Broad Spectrum SPF value of 15 or higher and other sun protection measures including:
- limit time in the sun, especially from 10 a.m. - 2 p.m.
- wear long-sleeve shirts, pants, hats, and sunglasses

Inactive ingredients

Acrylates/C10-30 Alkyl Acrylate Crosspolymer, Acrylates/Dimethicone Copolymer, Allantoin, Aluminum Starch Octenylsuccinate, Arachidyl Alcohol, Arachidyl Glucoside, Arginine, Behenyl Alcohol, Benzyl Alcohol, Bisabolol, Butylene Glycol, Butyrospermum Parkii (Shea) Butter, Camellia Sinensis Leaf Extract, Chlorphenesin, Cyclopentasiloxane, Dipropylene Glycol, Disodium EDTA, Ethylhexylglycerin, Fragrance/Parfum, Glycerin, Glyceryl Stearate, Hydrogenated Lecithin, Lauroyl Lysine, Lecithin, Maltodextrin, PEG-100 Stearate, PEG-40 Hydrogenated Castor Oil, Phenethyl Alcohol, Phenoxyethanol, Royal Jelly Powder, Royal Jelly, Silica, Styrene/Acrylates Copolymer, Tetrapeptide-45, Trideceth-9, Theobroma Cacao (Cocoa) Seed Extract, Water/Aqua, Zingiber Officinale (Ginger) Root Extract

Other information

Protect this product from excessive heat and direct sun